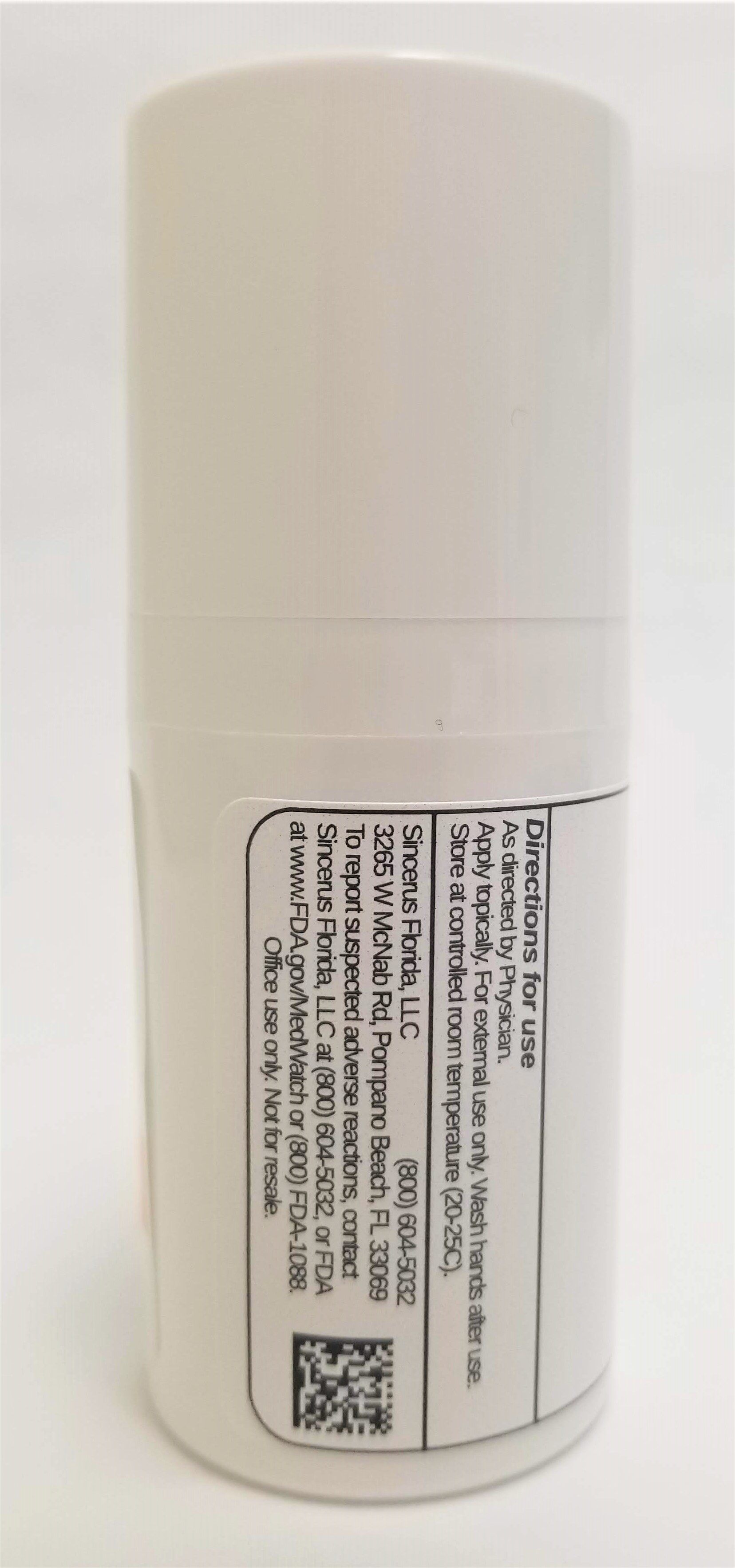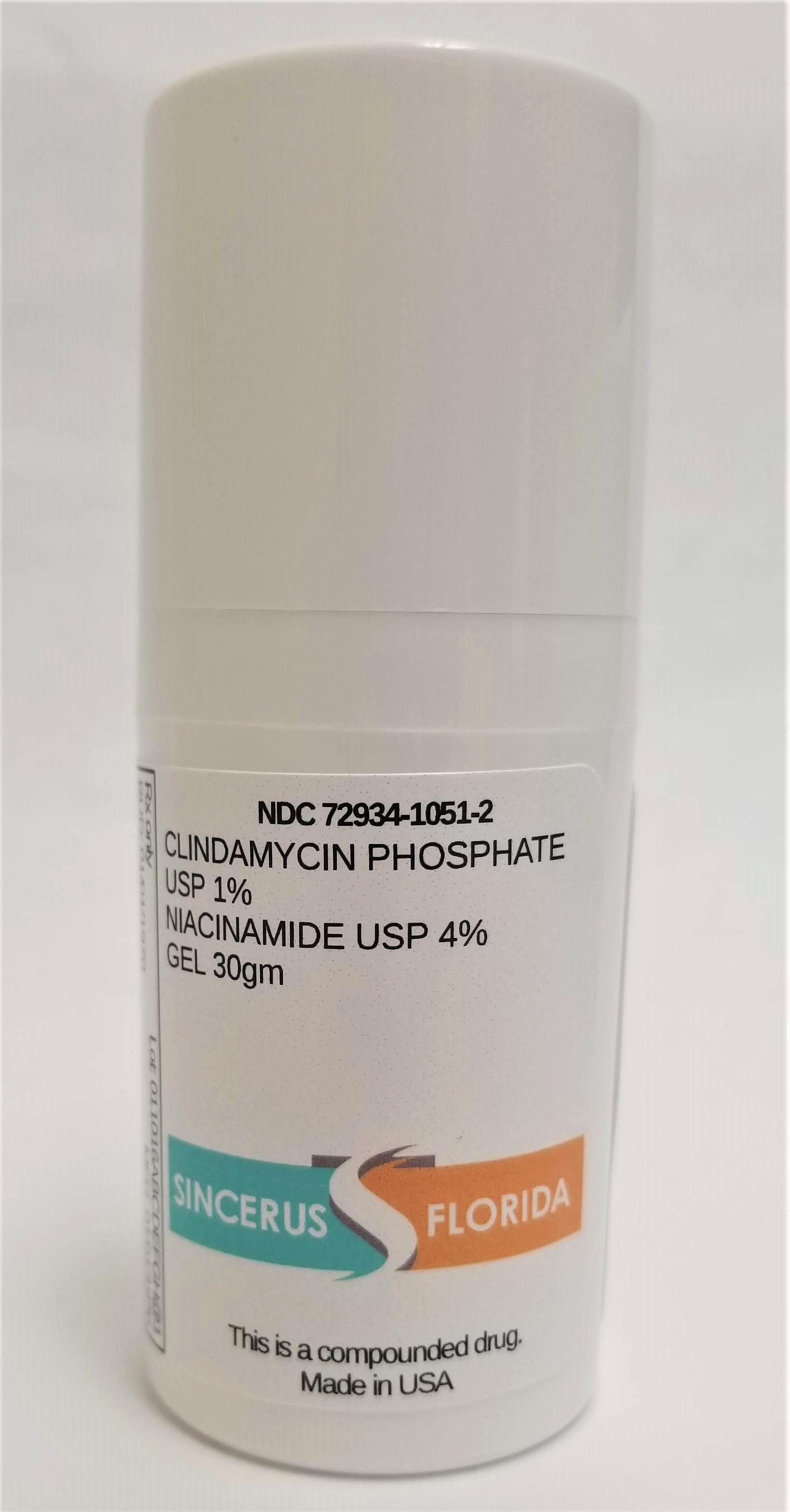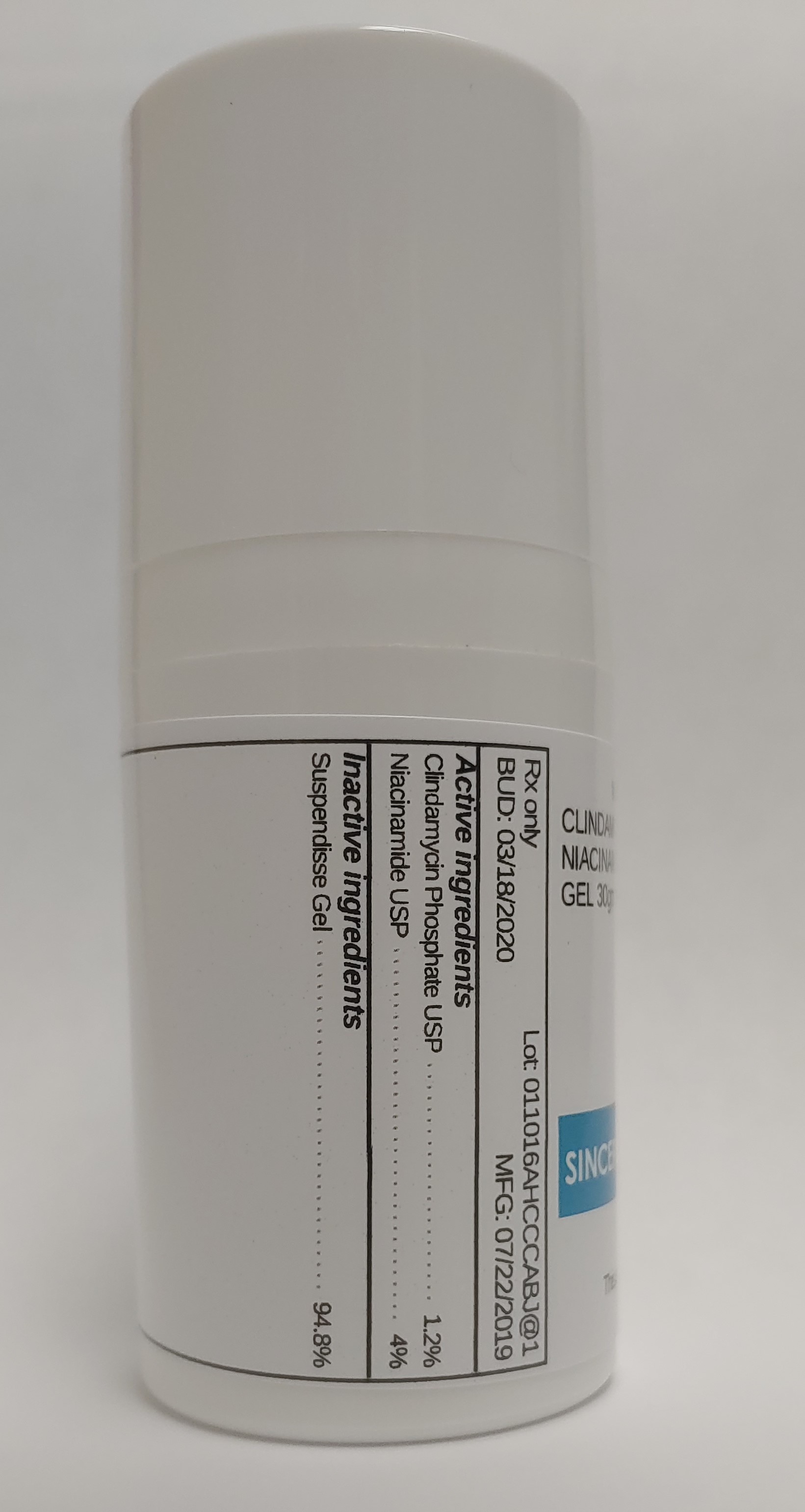 DRUG LABEL: CLINDAMYCIN 1% / NIACINAMIDE 4%
NDC: 72934-1051 | Form: GEL
Manufacturer: Sincerus Florida, LLC
Category: prescription | Type: HUMAN PRESCRIPTION DRUG LABEL
Date: 20190819

ACTIVE INGREDIENTS: NIACINAMIDE 4 g/100 g; CLINDAMYCIN PHOSPHATE 1 g/100 g

CLINDAMYCIN 1% / NIACINAMIDE 4%